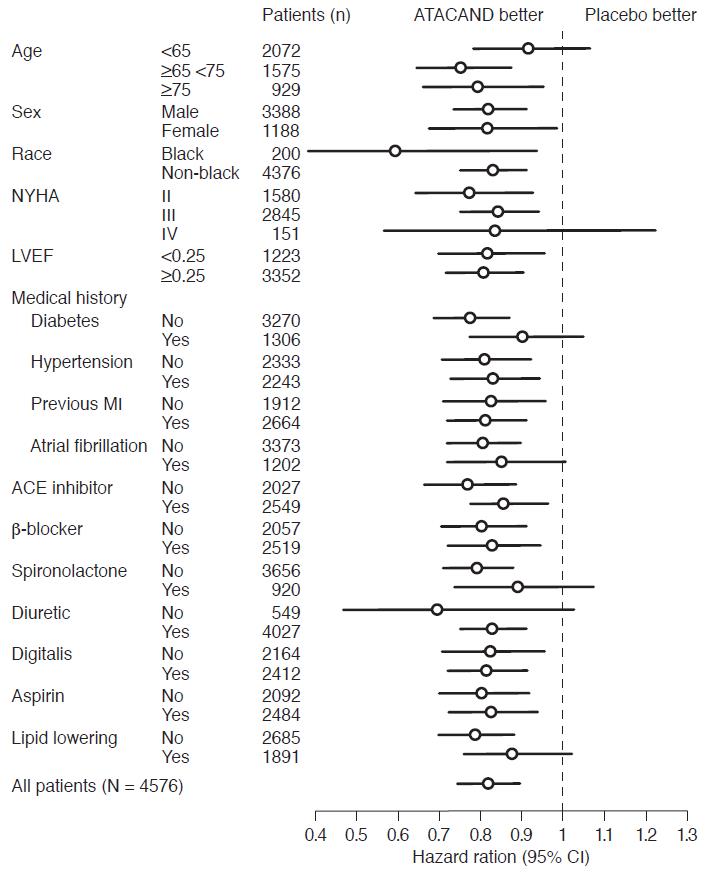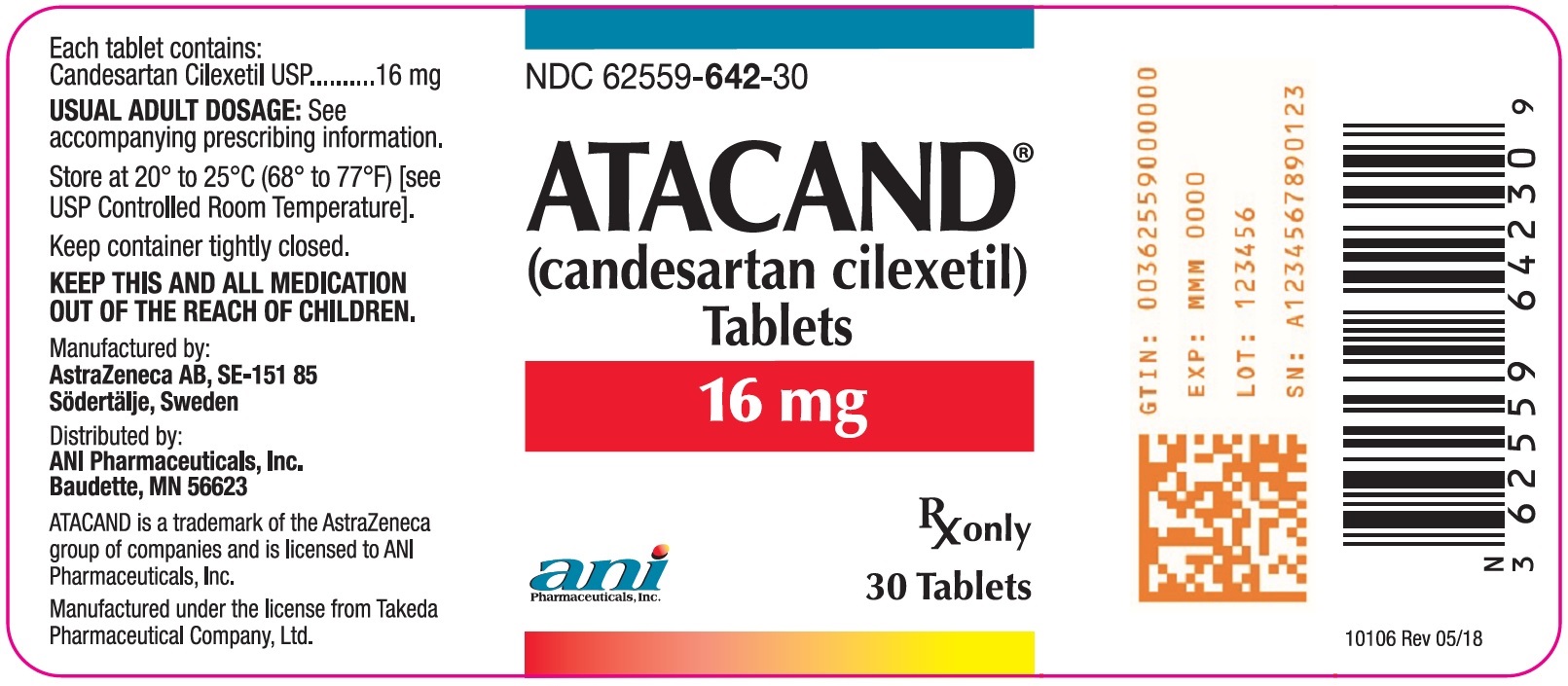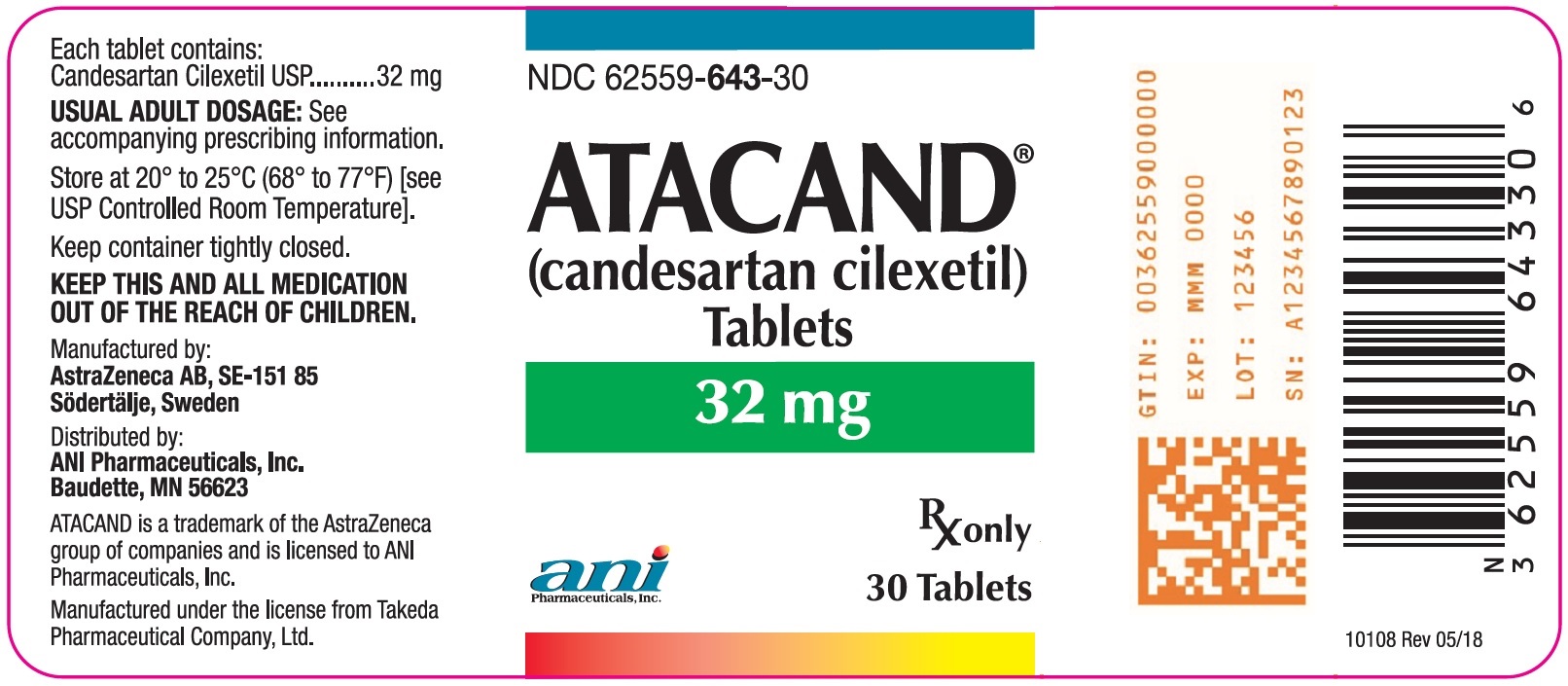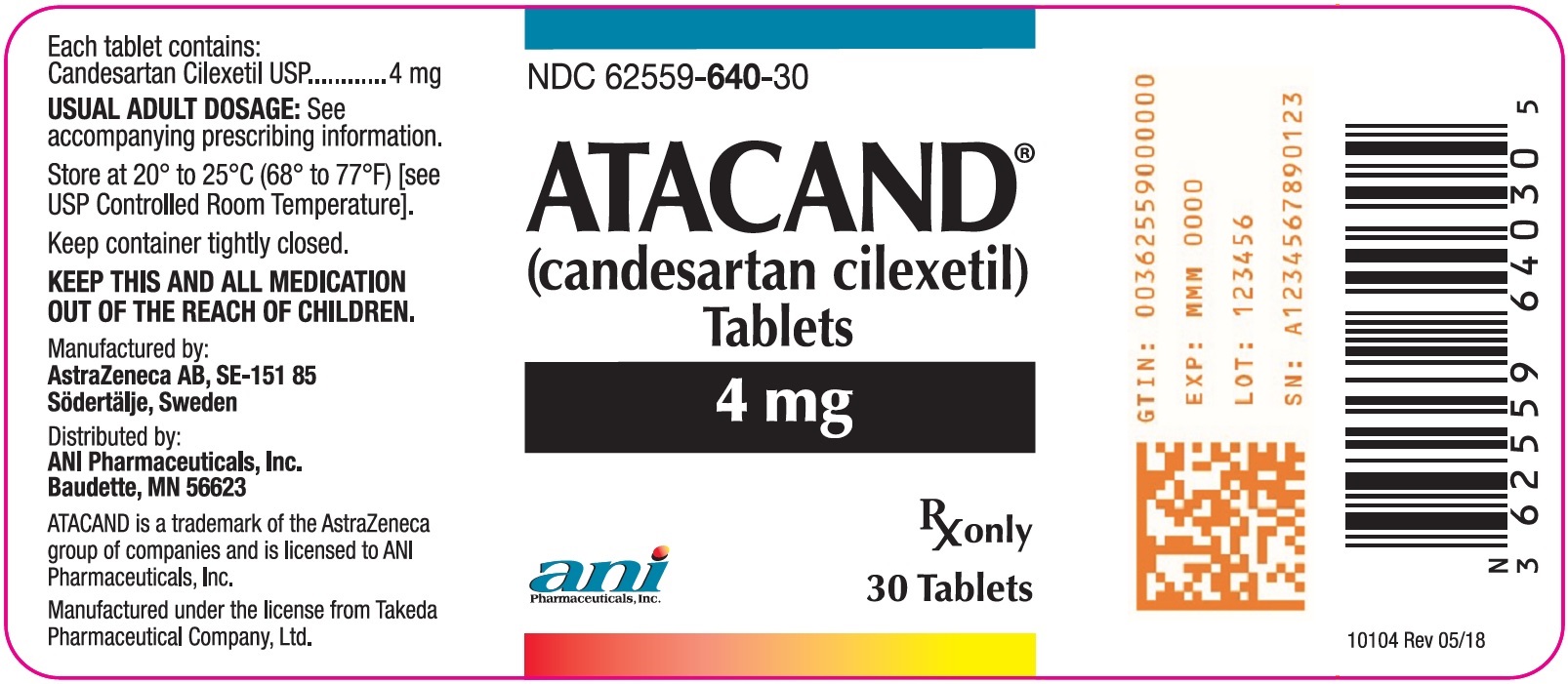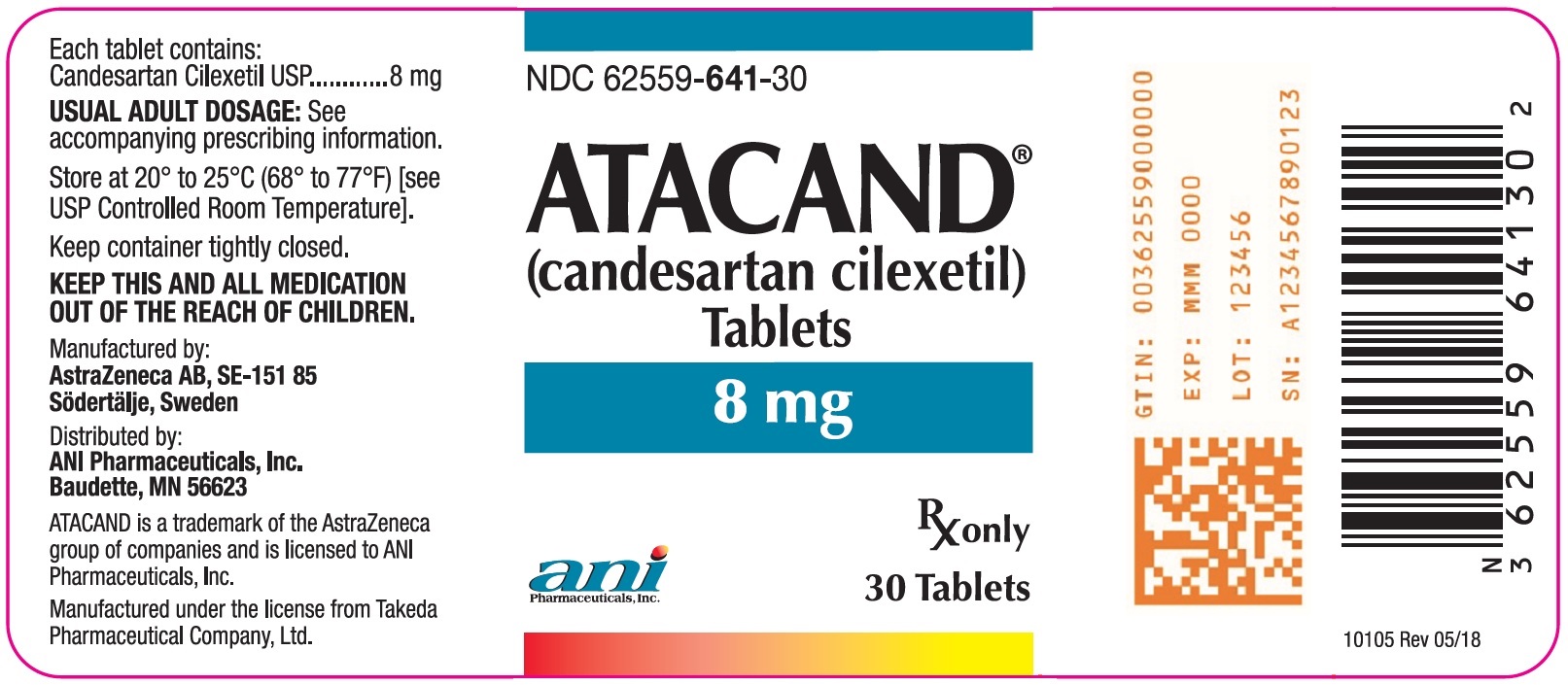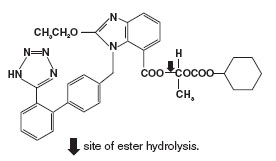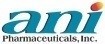 DRUG LABEL: ATACAND
NDC: 62559-640 | Form: TABLET
Manufacturer: ANI Pharmaceuticals, Inc.
Category: prescription | Type: HUMAN PRESCRIPTION DRUG LABEL
Date: 20251222

ACTIVE INGREDIENTS: CANDESARTAN CILEXETIL 4 mg/1 1
INACTIVE INGREDIENTS: HYDROXYPROPYL CELLULOSE, UNSPECIFIED; LACTOSE MONOHYDRATE; STARCH, CORN; CARBOXYMETHYLCELLULOSE CALCIUM; MAGNESIUM STEARATE; POLYETHYLENE GLYCOL 8000

HIGHLIGHTS OF PRESCRIBING INFORMATION

These highlights do not include all the information needed to use ATACAND safely and effectively. See full prescribing information for ATACAND.
ATACAND® (candesartan cilexetil) tablets, for oral use
Initial U.S. Approval: 1998

WARNING: FETAL TOXICITY

See full prescribing information for complete boxed warning.

- When pregnancy is detected, discontinue ATACAND as soon as possible. (5.1, 8.1)
- Drugs that act directly on the renin-angiotensin system can cause injury and death to the developing fetus. (5.1, 8.1)

1 INDICATIONS AND USAGE

ATACAND is an angiotensin II receptor blocker (ARB) indicated for:

- Treatment of hypertension in adults and children 1 to < 17 years of age, to lower blood pressure. Lowering blood pressure reduces the risk of fatal and non-fatal cardiovascular events, primarily strokes and myocardial infarctions (1.1).
- Treatment of heart failure (NYHA class II-IV); ATACAND reduces cardiovascular death and heart failure hospitalization (1.2).

2 DOSAGE AND ADMINISTRATION

 | Starting Dose | Target Dose
Adult Hypertension (2.1) | 16 mg tablet once daily | 8 – 32 mg tablet total daily dose
Pediatric Hypertension (1 to < 6 years) (2.2) | 0.20 mg/kg oral suspension once daily | 0.05 – 0.4 mg/kg oral suspension once daily or consider divided dose
Pediatric Hypertension (6 to < 17 years) (2.2) | < 50 kg 4 – 8 mg tablet once daily; >50 kg 8 – 16 mg tablet once daily | < 50 kg 4 – 16 mg tablet once daily or consider divided dose; > 50 kg 4 – 32 mg tablet once daily or consider divided dose
Adult Heart Failure (2.3) | 4 mg tablet once daily | 32 mg tablet once daily [The target dose is 32 mg once daily, which is achieved by doubling the dose at approximately 2-week intervals, as tolerated by patient.]

3 DOSAGE FORMS AND STRENGTHS

Tablets 4 mg, 8 mg, 16 mg, 32 mg (3).

4 CONTRAINDICATIONS

Known hypersensitivity to product components (4).

Do not co-administer aliskiren with ATACAND in patients with diabetes (4).

5 WARNINGS AND PRECAUTIONS

- Observe for signs and symptoms of hypotension (5.3).
- Monitor renal function (5.4) and potassium levels (5.5).

6 ADVERSE REACTIONS

- Most common adverse reactions which caused adult patients to discontinue therapy for:
  - Hypertension were headache (0.6%) and dizziness (0.3%) (6.1).
  - Heart Failure were hypotension (4.1%) (5.3), abnormal renal function (6.3%) (5.4), and hyperkalemia (2.4%) (5.5).

To report SUSPECTED ADVERSE REACTIONS, contact ANI Pharmaceuticals, Inc. at 1-855-204-1431 or FDA at 1-800-FDA-1088 or www.fda.gov/medwatch.

7 DRUG INTERACTIONS

- Lithium: Increases in serum lithium concentrations and toxicity (7).
- NSAIDs use may lead to increased risk of renal impairment and loss of antihypertensive effect (7).
- Combined inhibition of the renin-angiotensin system: Increased risk of renal impairment, hypotension, and hyperkalemia (7).

8 USE IN SPECIFIC POPULATIONS

- Nursing Mothers: Either nursing or drug should be discontinued (8.2).
- Pediatrics: Children < 1 year of age must not receive ATACAND for hypertension (5.2). Inhibitors of the renin-angiotensin system can cause renal abnormalities in neonatal animals (12.3).

FULL PRESCRIBING INFORMATION

WARNING: FETAL TOXICITY

- When pregnancy is detected, discontinue ATACAND as soon as possible [see Warnings and Precautions (5.1) and Use in Specific Populations (8.1)].
- Drugs that act directly on the renin-angiotensin system can cause injury and death to the developing fetus [see Warnings and Precautions (5.1) and Use in Specific Populations (8.1)].

1 INDICATIONS AND USAGE

1.1 Hypertension

ATACAND is indicated for the treatment of hypertension in adults and in children 1 to <17 years of age, to lower blood pressure. Lowering blood pressure reduces the risk of fatal and non-fatal cardiovascular events, primarily strokes and myocardial infarctions. These benefits have been seen in controlled trials of antihypertensive drugs from a wide variety of pharmacologic classes including the class to which this drug principally belongs.

Control of high blood pressure should be part of comprehensive cardiovascular risk management, including, as appropriate, lipid control, diabetes management, antithrombotic therapy, smoking cessation, exercise, and limited sodium intake. Many patients will require more than one drug to achieve blood pressure goals. For specific advice on goals and management, see published guidelines, such as those of the National High Blood Pressure Education Program’s Joint National Committee on Prevention, Detection, Evaluation, and Treatment of High Blood Pressure (JNC).

Numerous antihypertensive drugs, from a variety of pharmacologic classes and with different mechanisms of action, have been shown in randomized controlled trials to reduce cardiovascular morbidity and mortality, and it can be concluded that it is blood pressure reduction, and not some other pharmacologic property of the drugs, that is largely responsible for those benefits. The largest and most consistent cardiovascular outcome benefit has been a reduction in the risk of stroke, but reductions in myocardial infarction and cardiovascular mortality also have been seen regularly.

Elevated systolic or diastolic pressure causes increased cardiovascular risk, and the absolute risk increase per mmHg is greater at higher blood pressures, so that even modest reductions of severe hypertension can provide substantial benefit. Relative risk reduction from blood pressure reduction is similar across populations with varying absolute risk, so the absolute benefit is greater in patients who are at higher risk independent of their hypertension (for example, patients with diabetes or hyperlipidemia), and such patients would be expected to benefit from more aggressive treatment to a lower blood pressure goal.

Some antihypertensive drugs have smaller blood pressure effects (as monotherapy) in black patients, and many antihypertensive drugs have additional approved indications and effects (e.g., on angina, heart failure, or diabetic kidney disease). These considerations may guide selection of therapy.

ATACAND may be used alone or in combination with other antihypertensive agents.

1.2 Heart Failure

ATACAND is indicated for the treatment of heart failure (NYHA class II-IV) in adults with left ventricular systolic dysfunction (ejection fraction ≤ 40%) to reduce cardiovascular death and to reduce heart failure hospitalizations [see Clinical Studies (14.2)]. ATACAND also has an added effect on these outcomes when used with an ACE inhibitor [see Drug Interactions (7.4)].

2 DOSAGE AND ADMINISTRATION

2.1 Adult Hypertension

Dosage must be individualized. Blood pressure response is dose related over the range of 2 to 32 mg. The usual recommended starting dose of ATACAND is 16 mg once daily when it is used as monotherapy in patients who are not volume depleted. ATACAND can be administered once or twice daily with total daily doses ranging from 8 mg to 32 mg. Larger doses do not appear to have a greater effect, and there is relatively little experience with such doses. Most of the antihypertensive effect is present within 2 weeks, and maximal blood pressure reduction is generally obtained within 4 to 6 weeks of treatment with ATACAND.

Use in Hepatic Impairment: Initiate with 8 mg ATACAND in patients with moderate hepatic insufficiency. Dosing recommendations cannot be provided for patients with severe hepatic insufficiency [see Clinical Pharmacology (12.3)].

ATACAND may be administered with or without food.

If blood pressure is not controlled by ATACAND alone, a diuretic may be added. ATACAND may be administered with other antihypertensive agents.

2.2 Pediatric Hypertension 1 to < 17 Years of Age

ATACAND may be administered once daily or divided into two equal doses. Adjust the dosage according to blood pressure response. For patients with possible depletion of intravascular volume (e.g., patients treated with diuretics, particularly those with impaired renal function), initiate ATACAND under close medical supervision and consider administration of a lower dose [see Warnings and Precautions (5.3)].

Children 1 to < 6 years of age:

The dose range is 0.05 to 0.4 mg/kg per day. The recommended starting dose is 0.20 mg/kg (oral suspension).

Children 6 to < 17 years of age:

For those less than 50 kg, the dose range is 2 to 16 mg per day. The recommended starting dose is 4 to 8 mg.

For those greater than 50 kg, the dose range is 4 to 32 mg per day. The recommended starting dose is 8 to 16 mg.

Doses above 0.4 mg/kg (1 to < 6 year olds) or 32 mg (6 to < 17 year olds) have not been studied in pediatric patients [see Clinical Studies (14.1)].

An antihypertensive effect is usually present within 2 weeks, with full effect generally obtained within 4 weeks of treatment with ATACAND.

Children < 1 year of age must not receive ATACAND for hypertension.

All pediatric patients with a glomerular filtration rate less than 30 mL/min/1.73m^2 should not receive ATACAND since ATACAND has not been studied in this population [see Use in Specific Populations (8.4)].

For children who cannot swallow tablets, an oral suspension may be substituted as described below:

Preparation of Oral Suspension:

ATACAND oral suspension can be prepared in concentrations within the range of 0.1 to 2.0 mg/mL. Typically, a concentration of 1 mg/mL will be suitable for the prescribed dose. Any strength of ATACAND tablets can be used in the preparation of the suspension.

Follow the steps below for preparation of the suspension. The number of tablets and volume of vehicle specified below will yield 160 mL of a 1 mg/mL suspension.

- Prepare the vehicle by adding equal volumes of Ora-Plus® (80 mL) and Ora-Sweet SF® (80 mL) or, alternatively, use Ora-Blend SF® (160 mL).
- Add a small amount of vehicle to the required number of ATACAND tablets (five 32 mg tablets) and grind into a smooth paste using a mortar and pestle.
- Add the paste to a preparation vessel of suitable size.
- Rinse the mortar and pestle clean using the vehicle and add this to the vessel. Repeat, if necessary.
- Prepare the final volume by adding the remaining vehicle.
- Mix thoroughly.
- Dispense into suitably sized amber PET bottles.
- Label with an expiry date of 100 days and include the following instructions:

Store at room temperature (below 30°C/86°F). Use within 30 days after first opening. Do not use after the expiry date stated on the bottle.

Do not freeze.

Shake well before each use.

2.3 Adult Heart Failure

The recommended initial dose for treating heart failure is 4 mg once daily. The target dose is 32 mg once daily, which is achieved by doubling the dose at approximately 2-week intervals, as tolerated by the patient.

3 DOSAGE FORMS AND STRENGTHS

4 mg are white to off-white, circular/biconvex-shaped, non-film-coated scored tablets, coded ACF on one side and 004 on the other.

8 mg are light pink, circular/biconvex-shaped, non-film-coated scored tablets, coded ACG on one side and 008 on the other.

16 mg are pink, circular/biconvex-shaped, non-film-coated scored tablets, coded ACH on one side and 016 on the other.

32 mg are pink, circular/biconvex-shaped, non-film-coated scored tablets, coded ACL on one side and 032 on the other.

4 CONTRAINDICATIONS

ATACAND is contraindicated in patients who are hypersensitive to candesartan.

Do not co-administer aliskiren with ATACAND in patients with diabetes [see Drug Interactions (7.4)].

5 WARNINGS AND PRECAUTIONS

5.1 Fetal Toxicity

ATACAND can cause fetal harm when administered to a pregnant woman. Use of drugs that act on the renin-angiotensin system during the second and third trimesters of pregnancy reduces fetal renal function and increases fetal and neonatal morbidity and death. Resulting oligohydramnios can be associated with fetal lung hypoplasia and skeletal deformations. Potential neonatal adverse effects include skull hypoplasia, anuria, hypotension, renal failure and death. When pregnancy is detected, discontinue ATACAND as soon as possible [see Use in Specific Populations (8.1)].

5.2 Morbidity in Infants

Children < 1 year of age must not receive ATACAND for hypertension. Drugs that act directly on the renin-angiotensin system (RAS) can have effects on the development of immature kidneys.

5.3 Hypotension

ATACAND can cause symptomatic hypotension. Symptomatic hypotension is most likely to occur in patients who have been volume and/or salt depleted as a result of prolonged diuretic therapy, dietary salt restriction, dialysis, diarrhea, or vomiting. Patients with symptomatic hypotension may require temporarily reducing the dose of ATACAND, diuretic or both, and volume repletion. Volume and/or salt depletion should be corrected before initiating therapy with ATACAND.

In the CHARM program (heart failure patients), hypotension was reported in 18.8% of patients on ATACAND versus 9.8% of patients on placebo. The incidence of hypotension leading to drug discontinuation in ATACAND-treated patients was 4.1% compared with 2.0% in placebo-treated patients. In the CHARM-Added program, where candesartan or placebo was given in addition to ACE inhibitors, hypotension was reported in 22.6% of patients treated with ATACAND versus 13.8% treated with placebo [see Drug Interactions (7.3)].

Monitoring of blood pressure is recommended during dose escalation and periodically thereafter.

Major Surgery/Anesthesia

Hypotension may occur during major surgery and anesthesia in patients treated with angiotensin II receptor antagonists, including ATACAND, due to blockade of the renin-angiotensin system. Very rarely, hypotension may be severe such that it may warrant the use of intravenous fluids and/or vasopressors.

5.4 Impaired Renal Function

Monitor renal function periodically in patients treated with ATACAND. Changes in renal function including acute renal failure can be caused by drugs that inhibit the renin-angiotensin system. Patients whose renal function may depend, in part, on the activity of the renin-angiotensin system (e.g., patient with renal artery stenosis, chronic kidney disease, severe heart failure, or volume depletion) may be at particular risk of developing oliguria, progressive azotemia or acute renal failure when treated with ATACAND. Consider withholding or discontinuing therapy in patients who develop a clinically significant decrease in renal function on ATACAND.

In the CHARM program (heart failure patients), the incidence of abnormal renal function (e.g., creatinine increase) was 12.5% in patients treated with ATACAND versus 6.3% in patients treated with placebo. The incidence of abnormal renal function (e.g., creatinine increase) leading to drug discontinuation in ATACAND-treated patients was 6.3% compared with 2.9% in placebo-treated patients. In the CHARM-Added program, where candesartan or placebo was given in addition to ACE inhibitors, the incidence of abnormal renal function (e.g., creatinine increase) was 15% in patients treated with ATACAND versus 9% in patients treated with placebo [see Drug Interactions (7.3)].

5.5 Hyperkalemia

Drugs that inhibit the renin-angiotensin system can cause hyperkalemia.
Concomitant use of ATACAND with drugs that increase potassium levels may increase the risk of hyperkalemia [see Drug Interactions (7.1)].

Monitor serum potassium periodically.

In the CHARM program (heart failure patients), the incidence of hyperkalemia was 6.3% in patients treated with ATACAND versus 2.1% in patients treated with placebo. The incidence of hyperkalemia leading to drug discontinuation in ATACAND-treated patients was 2.4% compared with 0.6% in placebo-treated patients. In the CHARM-Added program where candesartan or placebo was given in addition to ACE inhibitors, the incidence of hyperkalemia was 9.5% in patients treated with ATACAND versus 3.5% in patients treated with placebo [see Drug Interactions (7.1)].

6 ADVERSE REACTIONS

6.1 Clinical Studies Experience

Because clinical studies are conducted under widely varying conditions, adverse reaction rates observed in the clinical studies of a drug cannot be directly compared to rates in the clinical studies of another drug and may not reflect the rates observed in practice.

Adult Hypertension

ATACAND has been evaluated for safety in more than 3600 patients/subjects, including more than 3200 patients treated for hypertension. About 600 of these patients were studied for at least 6 months and about 200 for at least 1 year. In general, treatment with ATACAND was well tolerated. The overall incidence of adverse events reported with ATACAND was similar to placebo.

The rate of withdrawals due to adverse events in all trials in patients (7510 total) was 3.3% (i.e., 108 of 3260) of patients treated with ATACAND as monotherapy and 3.5% (i.e., 39 of 1106) of patients treated with placebo. In placebo-controlled trials, discontinuation of therapy due to clinical adverse events occurred in 2.4% (i.e., 57 of 2350) of patients treated with ATACAND and 3.4% (i.e., 35 of 1027) of patients treated with placebo.

The most common reasons for discontinuation of therapy with ATACAND were headache (0.6%) and dizziness (0.3%).

The adverse events that occurred in placebo-controlled clinical trials in at least 1% of patients treated with ATACAND and at a higher incidence in candesartan cilexetil (n = 2350) than placebo (n = 1027) patients included back pain (3% vs. 2%), dizziness (4% vs. 3%), upper respiratory tract infection (6% vs. 4%), pharyngitis (2% vs. 1%), and rhinitis (2% vs. 1%).

Pediatric Hypertension

Among children in clinical studies, 1 in 93 children age 1 to < 6 and 3 in 240 age 6 to < 17 experienced worsening renal disease. The association between candesartan and exacerbation of the underlying condition could not be excluded.

Heart Failure

The adverse event profile of ATACAND in adult heart failure patients was consistent with the pharmacology of the drug and the health status of the patients. In the CHARM program, comparing ATACAND in total daily doses up to 32 mg once daily (n=3803) with placebo (n=3796), 21.0% of patients discontinued ATACAND for adverse events vs. 16.1% of placebo patients.

6.2 Postmarketing Experience

The following adverse reactions were identified during post-approval use of ATACAND. Because these reactions are reported voluntarily from a population of uncertain size, it is not always possible to reliably estimate their frequency or establish a causal relationship to drug exposure.

The following have been very rarely reported in post-marketing experience:

Digestive: Abnormal hepatic function and hepatitis.

Hematologic: Neutropenia, leukopenia, and agranulocytosis.

Immunologic: Angioedema

Metabolic and Nutritional Disorders: Hyperkalemia, hyponatremia.

Respiratory System Disorders: Cough.

Skin and Appendages Disorders: Pruritus, rash and urticaria.

Rare reports of rhabdomyolysis have been reported in patients receiving angiotensin II receptor blockers.

7 DRUG INTERACTIONS

7.1 Agents Increasing Serum Potassium

Co-administration of ATACAND with potassium sparing diuretics, potassium supplements, potassium-containing salt substitutes or other drugs that raise serum potassium levels may result in hyperkalemia. Monitor serum potassium in such patients.

7.2 Lithium

Increases in serum lithium concentrations and toxicity have been reported during concomitant administration of lithium with angiotensin II receptor antagonists, including ATACAND. Monitor serum lithium levels.

7.3 Non-Steroidal Anti-Inflammatory Agents Including Selective Cyclooxygenase-2 Inhibitors (COX-2 Inhibitors)

In patients who are elderly, volume-depleted (including those on diuretic therapy), or with compromised renal function, co-administration of NSAIDs, including selective COX-2 inhibitors, with angiotensin II receptor antagonists, including candesartan, may result in deterioration of renal function, including possible acute renal failure. These effects are usually reversible. Monitor renal function periodically in patients receiving candesartan and NSAID therapy.

The antihypertensive effect of angiotensin II receptor antagonists, including candesartan may be attenuated by NSAIDs including selective COX-2 inhibitors.

7.4 Combination Blockade of the Renin-Angiotensin System (RAS)

Dual blockade of the RAS with angiotensin receptor blockers, ACE inhibitors, or aliskiren is associated with increased risks of hypotension, hyperkalemia, and changes in renal function (including acute renal failure) compared to monotherapy. Triple combination of ATACAND with an ACE-inhibitor and a mineralocorticoid receptor antagonist is generally not recommended. Closely monitor blood pressure, renal function and electrolytes in patients on ATACAND and other agents that affect the RAS.

Do not co-administer aliskiren with ATACAND in patients with diabetes. Avoid use of aliskiren with ATACAND in patients with renal impairment (GFR <60 mL/min) [see Contraindications (4)].

8 USE IN SPECIFIC POPULATIONS

8.1 Pregnancy

Risk Summary

ATACAND can cause fetal harm when administered to a pregnant woman. Use of drugs that act on the renin-angiotensin system during the second and third trimesters of pregnancy reduces fetal renal function and increases fetal and neonatal morbidity and death. Most epidemiologic studies examining fetal abnormalities after exposure to antihypertensive use in the first trimester have not distinguished drugs affecting the renin-angiotensin system from other antihypertensive agents.

When pregnancy is detected, discontinue ATACAND as soon as possible.

The estimated background risk of major birth defects and miscarriage for the indicated population is unknown. All pregnancies have a background risk of birth defect, loss, or other adverse outcomes. In the U.S. general population, the estimated background risk of major birth defects and miscarriage in clinically recognized pregnancies is 2% to 4% and 15% to 20%, respectively.

Clinical Considerations

Disease-associated maternal and/or embryo/fetal risk

Hypertension in pregnancy increases the maternal risk for pre-eclampsia, gestational diabetes, premature delivery, and delivery complications (e.g., need for cesarean section, and post-partum hemorrhage). Hypertension increases the fetal risk for intrauterine growth restriction and intrauterine death. Pregnant women with hypertension should be carefully monitored and managed accordingly.

Pregnant women with chronic heart failure are at increased risk for preterm birth. Stroke volume and heart rate increase during pregnancy, increasing cardiac output, especially during the first trimester. Heart failure may worsen with pregnancy and may lead to maternal death. Closely monitor pregnant patients for destabilization of their heart failure.

Fetal/Neonatal Adverse Reactions

Oligohydramnios in pregnant women who use drugs affecting the renin-angiotensin system in the second and third trimesters of pregnancy can result in the following: reduced fetal renal function leading to anuria and renal failure fetal lung hypoplasia, skeletal deformations, including skull hypoplasia, hypotension and death. In the unusual case that there is no appropriate alternative to therapy with drugs affecting the renin-angiotensin system for a particular patient, apprise the mother of the potential risk to the fetus.

Perform serial ultrasound examinations to assess the intra-amniotic environment. Fetal testing may be appropriate, based on the week of pregnancy. Patients and physicians should be aware, however, that oligohydramnios may not appear until after the fetus has sustained irreversible injury. If oligohydramnios is observed, consider alternative drug treatment. Closely observe infants with histories of in utero exposure to ATACAND for hypotension, oliguria, hyperkalemia or other symptoms of renal impairment [see Use in Specific Populations (8.4)]. In neonates with a history of in utero exposure to ATACAND, if oliguria or hypotension occurs, support blood pressure and renal perfusion. Exchange transfusions or dialysis may be required as a means of reversing hypotension and replacing renal function.

Animal Data
Oral doses ≥10 mg of candesartan cilexetil/kg/day administered to pregnant rats during late gestation and continued through lactation were associated with reduced survival and an increased incidence of hydronephrosis in the offspring. The 10-mg/kg/day dose in rats is approximately 2.8 times the maximum recommended daily human dose (MRHD) of 32 mg on a mg/m^2 basis (comparison assumes human body weight of 50 kg). Candesartan cilexetil is toxic to rabbits. When given to pregnant rabbits at an oral dose of 3 mg/kg/day (approximately 1.7 times the MRHD on a mg/m^2 basis), candesartan cilexetil caused maternal toxicity (decreased body weight and death) but, in surviving dams, had no adverse effects on fetal survival, fetal weight, or external, visceral, or skeletal development. No maternal toxicity or adverse effects on fetal development were observed when oral doses up to 1000 mg of candesartan cilexetil/kg/day (approximately 138 times the MRHD on a mg/m^2 basis) were administered to pregnant mice.

8.2 Lactation

It is not known whether candesartan is excreted in human milk, but candesartan has been shown to be present in rat milk. Because of the potential for serious adverse reactions in breastfed infants, advise a nursing woman that breastfeeding is not recommended during treatment with ATACAND [see Warnings and Precautions (5.2)].

8.4 Pediatric Use

The antihypertensive effects of ATACAND were evaluated in hypertensive children 1 to < 17 years of age in randomized, double-blind clinical studies [see Clinical Studies (14.1)]. The pharmacokinetics of ATACAND have been evaluated in pediatric patients 1 to < 17 years of age [see Clinical Pharmacology (12.3)].

Children < 1 year of age must not receive ATACAND for hypertension [see Warnings and Precautions (5.2)].

10 OVERDOSAGE

No lethality was observed in acute toxicity studies in mice, rats, and dogs given single oral doses of up to 2000 mg/kg of candesartan cilexetil. In mice given single oral doses of the primary metabolite, candesartan, the minimum lethal dose was greater than 1000 mg/kg but less than 2000 mg/kg.

The most likely manifestation of overdosage with ATACAND would be hypotension, dizziness, and tachycardia; bradycardia could occur from parasympathetic (vagal) stimulation. If symptomatic hypotension should occur, supportive treatment should be instituted.

Candesartan cannot be removed by hemodialysis.

Treatment: To obtain up-to-date information about the treatment of overdose, consult your Regional Poison Control Center. Telephone numbers of certified poison control centers are listed in the Physicians’ Desk Reference (PDR). In managing overdose, consider the possibilities of multiple-drug overdoses, drug-drug interactions, and altered pharmacokinetics in your patient.

11 DESCRIPTION

ATACAND (candesartan cilexetil), a prodrug, is hydrolyzed to candesartan during absorption from the gastrointestinal tract. Candesartan is a selective AT1 subtype angiotensin II receptor antagonist.

Candesartan cilexetil, a nonpeptide, is chemically described as (±)-1-Hydroxyethyl 2-ethoxy-1-[p-(o-1H-tetrazol-5-ylphenyl)benzyl]-7-benzimidazolecarboxylate, cyclohexyl carbonate (ester).

Its empirical formula is C33H34N6O6, and its structural formula is:

Candesartan cilexetil is a white to off-white powder with a molecular weight of 610.67. It is practically insoluble in water and sparingly soluble in methanol. Candesartan cilexetil is a racemic mixture containing one chiral center at the cyclohexyloxycarbonyloxy ethyl ester group. Following oral administration, candesartan cilexetil undergoes hydrolysis at the ester link to form the active drug, candesartan, which is achiral.

ATACAND is available for oral use as tablets containing either 4 mg, 8 mg, 16 mg, or 32 mg of candesartan cilexetil and the following inactive ingredients: hydroxypropyl cellulose, polyethylene glycol, lactose, corn starch, carboxymethylcellulose calcium, and magnesium stearate. Ferric oxide (reddish brown) is added to the 8-mg, 16-mg, and 32-mg tablets as a colorant.

12 CLINICAL PHARMACOLOGY

12.1 Mechanism of Action

Angiotensin II is formed from angiotensin I in a reaction catalyzed by angiotensin-converting enzyme (ACE, kininase II). Angiotensin II is the principal pressor agent of the renin-angiotensin system, with effects that include vasoconstriction, stimulation of synthesis and release of aldosterone, cardiac stimulation, and renal reabsorption of sodium. Candesartan blocks the vasoconstrictor and aldosterone-secreting effects of angiotensin II by selectively blocking the binding of angiotensin II to the AT1 receptor in many tissues, such as vascular smooth muscle and the adrenal gland. Its action is, therefore, independent of the pathways for angiotensin II synthesis.

There is also an AT2 receptor found in many tissues, but AT2 is not known to be associated with cardiovascular homeostasis. Candesartan has much greater affinity (>10,000-fold) for the AT1 receptor than for the AT2 receptor.

Blockade of the renin-angiotensin system with ACE inhibitors, which inhibit the biosynthesis of angiotensin II from angiotensin I, is widely used in the treatment of hypertension. ACE inhibitors also inhibit the degradation of bradykinin, a reaction also catalyzed by ACE. Because candesartan does not inhibit ACE (kininase II), it does not affect the response to bradykinin. Whether this difference has clinical relevance is not yet known. Candesartan does not bind to or block other hormone receptors or ion channels known to be important in cardiovascular regulation.

Blockade of the angiotensin II receptor inhibits the negative regulatory feedback of angiotensin II on renin secretion, but the resulting increased plasma renin activity and angiotensin II circulating levels do not overcome the effect of candesartan on blood pressure.

12.2 Pharmacodynamics

Candesartan inhibits the pressor effects of angiotensin II infusion in a dose-dependent manner. After 1 week of once daily dosing with 8 mg of candesartan cilexetil, the pressor effect was inhibited by approximately 90% at peak with approximately 50% inhibition persisting for 24 hours.

Plasma concentrations of angiotensin I and angiotensin II, and plasma renin activity (PRA), increased in a dose-dependent manner after single and repeated administration of candesartan cilexetil to healthy subjects, hypertensive, and heart failure patients. ACE activity was not altered in healthy subjects after repeated candesartan cilexetil administration. The once-daily administration of up to 16 mg of candesartan cilexetil to healthy subjects did not influence plasma aldosterone concentrations, but a decrease in the plasma concentration of aldosterone was observed when 32 mg of candesartan cilexetil was administered to hypertensive patients. In spite of the effect of candesartan cilexetil on aldosterone secretion, very little effect on serum potassium was observed.

Hypertension

Adults

In multiple-dose studies with hypertensive patients, there were no clinically significant changes in metabolic function, including serum levels of total cholesterol, triglycerides, glucose, or uric acid. In a 12-week study of 161 patients with non-insulin-dependent (type 2) diabetes mellitus and hypertension, there was no change in the level of HbA1c.

Heart Failure

In heart failure patients, candesartan ≥ 8 mg resulted in decreases in systemic vascular resistance and pulmonary capillary wedge pressure.

12.3 Pharmacokinetics

Distribution

The volume of distribution of candesartan is 0.13 L/kg. Candesartan is highly bound to plasma proteins (>99%) and does not penetrate red blood cells. The protein binding is constant at candesartan plasma concentrations well above the range achieved with recommended doses. In rats, it has been demonstrated that candesartan crosses the blood-brain barrier poorly, if at all. It has also been demonstrated in rats that candesartan passes across the placental barrier and is distributed in the fetus.

Metabolism and Excretion

Because candesartan is not significantly metabolized by the cytochrome P450 system and at therapeutic concentrations has no effects on P450 enzymes, interactions with drugs that inhibit or are metabolized by those enzymes would not be expected.

Total plasma clearance of candesartan is 0.37 mL/min/kg, with a renal clearance of 0.19 mL/min/kg. When candesartan is administered orally, about 26% of the dose is excreted unchanged in urine. Following an oral dose of ^14C-labeled candesartan cilexetil, approximately 33% of radioactivity is recovered in urine and approximately 67% in feces. Following an intravenous dose of ^14C-labeled candesartan, approximately 59% of radioactivity is recovered in urine and approximately 36% in feces. Biliary excretion contributes to the elimination of candesartan.

Adults

Candesartan cilexetil is rapidly and completely bioactivated by ester hydrolysis during absorption from the gastrointestinal tract to candesartan, a selective AT1 subtype angiotensin II receptor antagonist. Candesartan is mainly excreted unchanged in urine and feces (via bile). It undergoes minor hepatic metabolism by O-deethylation to an inactive metabolite. The elimination half-life of candesartan is approximately 9 hours. After single and repeated administration, the pharmacokinetics of candesartan are linear for oral doses up to 32 mg of candesartan cilexetil. Candesartan and its inactive metabolite do not accumulate in serum upon repeated once-daily dosing.

Following administration of candesartan cilexetil, the absolute bioavailability of candesartan was estimated to be 15%. After tablet ingestion, the peak serum concentration (Cmax) is reached after 3 to 4 hours. Food with a high fat content does not affect the bioavailability of candesartan after candesartan cilexetil administration.

Pediatrics

In children 1 to 17 years of age, plasma levels are greater than 10–fold higher at peak (approximately 4 hours) than 24 hours after a single dose.

Children 1 to < 6 years of age, given 0.2 mg/kg had exposure similar to adults given 8 mg.

Children > 6 years of age had exposure similar to adults given the same dose.

The pharmacokinetics (Cmax and AUC) were not modified by age, sex or body weight.

Candesartan cilexetil pharmacokinetics have not been investigated in pediatric patients less than 1 year of age.

From the dose-ranging studies of candesartan cilexetil, there was a dose related increase in plasma candesartan concentrations.

The renin-angiotensin system (RAS) plays a critical role in kidney development. RAS blockade has been shown to lead to abnormal kidney development in very young mice. Children < 1 year of age must not receive ATACAND. Administering drugs that act directly on the renin-angiotensin system (RAS) can alter normal renal development.

Geriatric and Sex

The pharmacokinetics of candesartan have been studied in the elderly (≥ 65 years) and in both sexes. The plasma concentration of candesartan was higher in the elderly (Cmax was approximately 50% higher, and AUC was approximately 80% higher) compared to younger subjects administered the same dose. The pharmacokinetics of candesartan were linear in the elderly, and candesartan and its inactive metabolite did not accumulate in the serum of these subjects upon repeated, once-daily administration. No initial dosage adjustment is necessary [see Dosage and Administration (2.1)]. There is no difference in the pharmacokinetics of candesartan between male and female subjects.

Renal Insufficiency

In hypertensive patients with renal insufficiency, serum concentrations of candesartan were elevated. After repeated dosing, the AUC and Cmax were approximately doubled in patients with severe renal impairment (creatinine clearance <30 mL/min/1.73m^2) compared to patients with normal kidney function. The pharmacokinetics of candesartan in hypertensive patients undergoing hemodialysis are similar to those in hypertensive patients with severe renal impairment. Candesartan cannot be removed by hemodialysis. No initial dosage adjustment is necessary in patients with renal insufficiency [see Dosage and Administration (2.1)].

In heart failure patients with renal impairment, AUC0-72h was 36% and 65% higher in mild and moderate renal impairment, respectively. Cmax was 15% and 55% higher in mild and moderate renal impairment, respectively.

Pediatrics

ATACAND pharmacokinetics have not been determined in children with renal insufficiency.

Hepatic Insufficiency

The pharmacokinetics of candesartan were compared in patients with mild and moderate hepatic impairment to matched healthy volunteers following a single oral dose of 16 mg candesartan cilexetil. The increase in AUC for candesartan was 30% in patients with mild hepatic impairment (Child-Pugh A) and 145% in patients with moderate hepatic impairment (Child-Pugh B). The increase in Cmax for candesartan was 56% in patients with mild hepatic impairment and 73% in patients with moderate hepatic impairment. The pharmacokinetics after candesartan cilexetil administration have not been investigated in patients with severe hepatic impairment. No initial dosage adjustment is necessary in patients with mild hepatic impairment. In hypertensive patients with moderate hepatic impairment, consideration should be given to initiation of ATACAND at a lower dose [see Dosage and Administration (2.1)].

Heart Failure

The pharmacokinetics of candesartan were linear in patients with heart failure (NYHA class II and III) after candesartan cilexetil doses of 4, 8, and 16 mg. After repeated dosing, the AUC was approximately doubled in these patients compared with healthy, younger patients. The pharmacokinetics in heart failure patients is similar to that in healthy elderly volunteers [see Dosage and Administration (2.3)].

13 NONCLINICAL TOXICOLOGY

13.1 Carcinogenesis, Mutagenesis, Impairment of Fertility

There was no evidence of carcinogenicity when candesartan cilexetil was orally administered to mice and rats for up to 104 weeks at doses up to 100 and 1000 mg/kg/day, respectively. Rats received the drug by gavage, whereas mice received the drug by dietary administration. These (maximally-tolerated) doses of candesartan cilexetil provided systemic exposures to candesartan (AUCs) that were, in mice, approximately 7 times and, in rats, more than 70 times the exposure in man at the maximum recommended daily human dose (32 mg).

Candesartan and its O-deethyl metabolite tested positive for genotoxicity in the in vitro Chinese hamster lung (CHL) chromosomal aberration assay. Neither compound tested positive in the Ames microbial mutagenesis assay or the in vitro mouse lymphoma cell assay. Candesartan (but not its O-deethyl metabolite) was also evaluated in vivo in the mouse micronucleus test and in vitro in the Chinese hamster ovary (CHO) gene mutation assay, in both cases with negative results. Candesartan cilexetil was evaluated in the Ames test, the in vitro mouse lymphoma cell and rat hepatocyte unscheduled DNA synthesis assays and the in vivo mouse micronucleus test, in each case with negative results. Candesartan cilexetil was not evaluated in the CHL chromosomal aberration or CHO gene mutation assay.

Fertility and reproductive performance were not affected in studies with male and female rats given oral doses of up to 300 mg/kg/day (83 times the maximum daily human dose of 32 mg on a body surface area basis).

14 CLINICAL STUDIES

14.1 Hypertension

Adult

The antihypertensive effects of ATACAND were examined in 14 placebo-controlled trials of 4- to 12-weeks duration, primarily at daily doses of 2 to 32 mg per day in patients with baseline diastolic blood pressures of 95 to 114 mm Hg. Most of the trials were of candesartan cilexetil as a single agent, but it was also studied as add-on to hydrochlorothiazide and amlodipine. These studies included a total of 2350 patients randomized to one of several doses of candesartan cilexetil and 1027 to placebo. Except for a study in diabetics, all studies showed significant effects, generally dose related, of 2 to 32 mg on trough (24 hour) systolic and diastolic pressures compared to placebo, with doses of 8 to 32 mg giving effects of about 8-12/4-8 mm Hg. There were no exaggerated first-dose effects in these patients. Most of the antihypertensive effect was seen within 2 weeks of initial dosing and the full effect in 4 weeks. With once-daily dosing, blood pressure effect was maintained over 24 hours, with trough to peak ratios of blood pressure effect generally over 80%. Candesartan cilexetil had an additional blood pressure lowering effect when added to hydrochlorothiazide.

The antihypertensive effects of candesartan cilexetil and losartan potassium at their highest recommended doses administered once-daily were compared in two randomized, double-blind trials. In a total of 1268 patients with mild to moderate hypertension who were not receiving other antihypertensive therapy, candesartan cilexetil 32 mg lowered systolic and diastolic blood pressure by 2 to 3 mm Hg on average more than losartan potassium 100 mg, when measured at the time of either peak or trough effect. The antihypertensive effects of twice daily dosing of either candesartan cilexetil or losartan potassium were not studied.

The antihypertensive effect was similar in men and women and in patients older and younger than 65. Candesartan was effective in reducing blood pressure regardless of race, although the effect was somewhat less in blacks (usually a low-renin population). This has been generally true for angiotensin II antagonists and ACE inhibitors.

In long-term studies of up to 1 year, the antihypertensive effectiveness of candesartan cilexetil was maintained, and there was no rebound after abrupt withdrawal.

There were no changes in the heart rate of patients treated with candesartan cilexetil in controlled trials.

Pediatric

The antihypertensive effects of ATACAND were evaluated in hypertensive children 1 to < 6 years old and 6 to < 17 years of age in two randomized, double-blind multicenter, 4-week dose ranging studies. There were 93 patients 1 to < 6 years of age, 74% of whom had renal disease, that were randomized to receive an oral dose of candesartan cilexetil suspension 0.05, 0.20 or 0.40 mg/kg once daily. The primary method of analysis was slope of the change in systolic blood pressure (SBP) as a function of dose. Since there was no placebo group, the change from baseline likely overestimates the true magnitude of blood pressure effect. Nevertheless, SBP and diastolic blood pressure (DBP) decreased 6.0/5.2 to 12.0/11.1 mmHg from baseline across the three doses of candesartan.

In children 6 to < 17 years, 240 patients were randomized to receive either placebo or low, medium, or high doses of ATACAND in a ratio of 1: 2: 2: 2. For children who weighed < 50 kg the doses of ATACAND were 2, 8, or 16 mg once daily. For those > 50 kg the ATACAND doses were 4, 16 or 32 mg once daily. Those enrolled were 47% Black and 29% were female; mean age +/- SD was 12.9 +/- 2.6 years.

The placebo subtracted effect at trough for sitting systolic blood pressure/sitting diastolic blood pressure for the different doses were from 4.9/3.0 to 7.5/6.2 mmHg.

In children 6 to < 17 years there was a trend for a lesser blood pressure effect for Blacks compared to other patients. There were too few individuals in the age group of 1 - 6 years old to determine whether Blacks respond differently than other patients to ATACAND.

14.2 Heart Failure

Candesartan was studied in two heart failure outcome studies: 1. The Candesartan in Heart failure: Assessment of Reduction in Mortality and morbidity trial in patients intolerant of ACE inhibitors (CHARM–Alternative), 2. CHARM–Added in patients already receiving ACE inhibitors. Both studies were international double-blind, placebo-controlled trials in patients with NYHA class II - IV heart failure and LVEF ≤40%. In both trials, patients were randomized to placebo or ATACAND (initially 4-8 mg once daily, titrated as tolerated to 32 mg once daily) and followed for up to 4 years. Patients with serum creatinine > 3 mg/dL, serum potassium > 5.5 mEq/L, symptomatic hypotension or known bilateral renal artery stenosis were excluded. The primary end point in both trials was time to either cardiovascular death or hospitalization for heart failure.

CHARM–Alternative included 2028 subjects not receiving an ACE inhibitor due to intolerance. The mean age was 67 years and 32% were female, 48% were NYHA II, 49% were NYHA III, 4% were NYHA IV, and the mean ejection fraction was 30%. Sixty-two percent had a history of myocardial infarction, 50% had a history of hypertension, and 27% had diabetes. Concomitant drugs at baseline were diuretics (85%), digoxin (46%), beta-blockers (55%), and spironolactone (24%). The mean daily dose of ATACAND was approximately 23 mg and 59% of subjects on treatment received 32 mg once daily.

After a median follow-up of 34 months, there was a 23% reduction in the risk of cardiovascular death or heart failure hospitalization on ATACAND (p<0.001), with both components contributing to the overall effect (Table 1).

Table 1. CHARM — Alternative: Primary Endpoint and its Components
Endpoint (time to first event) | ATACAND; (n= 1013) | Placebo; (n=1015) | Hazard Ratio; (95% CI) | p-value; (logrank)
CV death or heart failure hospitalization | 334 | 406 | 0.77; (0.67–0.89) | <0.001
CV death | 219 | 252 | 0.85; (0.71–1.02) | 0.072
Heart failure hospitalization | 207 | 286 | 0.68; (0.57–0.81) | <0.001

In CHARM–Added, 2548 subjects receiving an ACE inhibitor were randomized to ATACAND or placebo. The specific ACE inhibitor and dose were at the discretion of the investigators, who were encouraged to titrate patients to doses known to be effective in clinical outcome trials, subject to patient tolerability. Forced titration to maximum tolerated doses of ACE inhibitor was not required.

The mean age was 64 years and 21% were female, 24% were NYHA II, 73% were NYHA III, 3% were NYHA IV, and the mean ejection fraction was 28%. Fifty-six percent had a history of myocardial infarction, 48% had a history of hypertension, and 30% had diabetes. Concomitant drugs at baseline in addition to ACE inhibitors were diuretics (90%), digoxin (58%), beta-blockers (55%), and spironolactone (17%). The mean daily dose of ATACAND was approximately 24 mg and 61% of subjects on treatment received 32 mg once daily.

After a median follow-up of 41 months, there was a 15% reduction in the risk of cardiovascular death or heart failure hospitalization on ATACAND (p=0.011), with both components contributing to the overall effect (Table 2). There was no evident relationship between dose of ACE inhibitor and the benefit of ATACAND.

Table 2. CHARM — Added: Primary Endpoint and its Components
Endpoint (time to first event) | ATACAND (n=1276) | Placebo (n=1272) | Hazard Ratio (95% CI) | p-value (logrank)
CV death or heart failure hospitalization | 483 | 538 | 0.85 (0.75–0.96) | 0.011
CV death | 302 | 347 | 0.84 (0.72–0.98) | 0.029
Heart failure hospitalization | 309 | 356 | 0.83 (0.71–0.96) | 0.014

In these two studies, the benefit of ATACAND in reducing the risk of CV death or heart failure hospitalization (18% p<0.001) was evident in major subgroups (see Figure), and in patients on other combinations of cardiovascular and heart failure treatments, including ACE inhibitors and beta-blockers.

Figure. CV Death or Heart Failure Hospitalization in Subgroups – LV Systolic Dysfunction Trials

16 HOW SUPPLIED/STORAGE AND HANDLING

ATACAND Tablets, 4 mg, are white to off-white, circular/biconvex-shaped, non-film-coated scored tablets, coded ACF on one side and 004 on the other. They are supplied in bottles of 30 tablets (NDC 62559-640-30).

ATACAND Tablets, 8 mg, are light pink, circular/biconvex-shaped, non-film-coated scored tablets, coded ACG on one side and 008 on the other. They are supplied in bottles of 30 tablets (NDC 62559-641-30).

ATACAND Tablets, 16 mg, are pink, circular/biconvex-shaped, non-film-coated scored tablets, coded ACH on one side and 016 on the other. They are supplied in bottles of 30 tablets (NDC 62559-642-30) and bottles of 90 tablets (NDC 62559-642-90).

ATACAND Tablets, 32 mg, are pink, circular/biconvex-shaped, non-film-coated scored tablets, coded ACL on one side and 032 on the other. They are supplied in bottles of 30 tablets (NDC 62559-643-30) and bottles of 90 tablets (NDC 62559-643-90).

Storage

Store at 20° to 25°C (68° to 77°F); excursions permitted at 15° to 30°C (59° to 86°F) [see USP Controlled Room Temperature]. Keep container tightly closed.

17 PATIENT COUNSELING INFORMATION

Advise patient to read FDA-approved patient labeling (Patient Information).

Pregnancy

Advise female patients of childbearing age about the consequences of exposure to ATACAND during pregnancy. Discuss treatment options with women planning to become pregnant. Tell patients to report pregnancies to their physicians as soon as possible.

Manufactured under the license from Takeda Pharmaceutical Company, Ltd.

Manufactured by:
AstraZeneca AB
SE-151 85 Södertälje, Sweden

Distributed by:
ANI Pharmaceuticals, Inc.
Baudette, MN 56623

ATACAND is a registered trademark of the AstraZeneca group of companies and is licensed to ANI Pharmaceuticals, Inc.

10110 Rev 07/25

Patient Information

ATACAND® (at-a-cand)
(candesartan cilexetil)
Tablets

Read the Patient Information that comes with ATACAND before you start taking it and each time you get a refill. There may be new information. This leaflet does not take the place of talking with your doctor about your medical condition or your treatment. If you have any questions about ATACAND, ask your doctor or pharmacist.

What is the most important information I should know about ATACAND?

ATACAND can cause harm or death to an unborn baby. Talk to your doctor about other ways to lower your blood pressure if you plan to become pregnant. If you get pregnant while taking ATACAND, tell your doctor right away.

What is ATACAND?

ATACAND is a prescription medicine called an angiotensin receptor blocker (ARB).

ATACAND is used to:

- treat high blood pressure in adults and children, 1 to 17 years of age
- treat certain types of heart failure in adults, to reduce death and hospitalization for heart damage and heart failure

Heart failure is a condition where the heart does not pump blood as well as it should.

ATACAND must not be used in children less than 1 year of age for high blood pressure.

Who should not take ATACAND?

Do not take ATACAND if you:

- are allergic to any of the ingredients in ATACAND. See the end of this leaflet for a complete list of ingredients in ATACAND.
- are diabetic and taking aliskiren.

What should I tell my doctor before taking ATACAND?

Before you take ATACAND, tell your doctor if you:

- have heart problems
- have liver problems
- have kidney problems
- currently have vomiting or diarrhea
- are scheduled for surgery or anesthesia. Low blood pressure can happen in people who take ATACAND and have major surgery and anesthesia.
- have any other medical conditions
- are pregnant or planning to become pregnant. See “What is the most important information I should know about ATACAND?”
- are breast-feeding or plan to breast-feed. It is not known if ATACAND passes into your breast milk. You and your doctor should decide if you will take ATACAND or breast-feed. You should not do both.

Tell your doctor about all the medicines you take, including prescription and non-prescription medicines, vitamins and herbal supplements. ATACAND and other medicines may affect each other causing serious side effects. ATACAND may affect the way other medicines work, and other medicines may affect how ATACAND works.

Especially tell your doctor if you take:

- lithium carbonate (Lithobid) or lithium citrate, medicines used in some types of depression
- other medicines for high blood pressure, especially water pills (diuretics)
- potassium supplements
- salt substitutes
- non-steroidal anti-inflammatory drugs (NSAIDs)

Know the medicines you take. Keep a list of your medications with you to show your doctor and pharmacist when a new medication is prescribed. Talk to your doctor or pharmacist before you start taking any new medicine. Your doctor or pharmacist will know what medicines are safe to take together.

How should I take ATACAND?

- Take ATACAND exactly as prescribed by your doctor.
- Do not change your dose or stop ATACAND without talking to your doctor, even if you are feeling well.
- If your child cannot swallow tablets, or if tablets are not available in the prescribed strength, your pharmacist will prepare ATACAND as a liquid suspension for your child. If your child switches between taking the tablet and the suspension, your doctor will change the dose as needed. Shake the bottle of suspension well before each dose.
- ATACAND is taken by mouth with or without food.
- If you miss a dose of ATACAND, take it as soon as you remember. If it is almost time for your next dose, skip the missed dose. Take the next dose on time. Do not take 2 doses at one time. If you are not sure about your dosing call your doctor or pharmacist.
- If you take more ATACAND than prescribed, call your doctor, local poison control center, or go to the nearest emergency room.

What should I avoid while taking ATACAND?

ATACAND can cause you to feel dizzy or tired. Do not drive, operate machinery, or do other dangerous activities until you know how ATACAND affects you.

What are the possible side effects of ATACAND?

ATACAND may cause serious side effects, including:

- Injury or death to your unborn baby. See “What is the most important information I should know about ATACAND?”
- Low blood pressure (hypotension). Low blood pressure is most likely to happen if you:
  - take water pills (diuretics)
  - are on a low salt diet
  - get dialysis treatments
  - are dehydrated (decreased body fluids) due to vomiting and diarrhea
  - have heart problems

If you feel dizzy or faint lie down and call your doctor right away.

Low blood pressure can also happen if you have major surgery or anesthesia. You will be monitored for this and treated if needed. See “What should I tell my doctor before taking ATACAND?”

- Worsening kidney problems. Kidney problems may get worse in people that already have kidney disease or heart problems. Your doctor may do blood tests to check for this.
- Increased potassium in your blood. Your doctor may do a blood test to check your potassium levels as needed.
- Symptoms of allergic reaction. Call your doctor right away if you have any of these symptoms of an allergic reaction:
  - swelling of your face, lips, tongue or throat
  - rash
  - hives and itching

The most common side effects of ATACAND are:

- back pain
- dizziness
- cold or flu symptoms (upper respiratory tract infection)
- sore throat (pharyngitis)
- nasal congestion and stuffiness (rhinitis)

Tell your doctor or pharmacist about any side effect that bothers you or that does not go away.

These are not all the side effects of ATACAND. Ask your doctor or pharmacist for more information.

Call your doctor for medical advice about side effects. You can report side effects to FDA at 1-800-FDA-1088.

How should I store ATACAND?

- Do not keep medicine that is out of date or that you no longer need.
- Store ATACAND tablets at room temperature below 86°F (30°C).
- Store ATACAND oral suspension at room temperature below 86°F (30°C).
- Use the oral suspension within 30 days after first opening the bottle. Do not use after the expiration date stated on the bottle.
- Do not freeze.
- Keep the container of ATACAND closed tightly.

Keep ATACAND and all medicine out of the reach of children.

General information about ATACAND

Medicines are sometimes prescribed for conditions that are not mentioned in patient information leaflets. Do not use ATACAND for a condition for which it was not prescribed. Do not give ATACAND to other people, even if they have the same problem you have. It may harm them.

This leaflet summarizes the most important information about ATACAND. If you would like more information, talk with your doctor. You can ask your doctor or pharmacist for information about ATACAND that is written for health professionals.

For more information, visit www.anipharmaceuticals.com or call 1-855-204-1431.

What are the ingredients in ATACAND?

Active ingredient: candesartan cilexetil.

Inactive ingredients in ATACAND tablets and ATACAND oral suspension are: hydroxypropyl cellulose, polyethylene glycol, lactose, corn starch, carboxymethylcellulose calcium, and magnesium stearate. Ferric oxide (reddish brown) is added to the 8-mg, 16-mg, and 32-mg tablets as a colorant.

In addition to the above, ATACAND oral suspension also includes the following inactive ingredients: Ora Plus, Ora Sweet or Ora-Blend.

How does ATACAND work?

ATACAND is a type of medicine called angiotensin receptor blocker, which blocks the effect of the hormone angiotensin II, causing the blood vessels to relax. This helps lower blood pressure. Medicines that lower your blood pressure lower your chance of having a stroke or heart attack.

This Patient Information has been approved by the U.S. Food and Drug Administration.

Manufactured under the license from Takeda Pharmaceutical Company, Ltd.

Manufactured by:
AstraZeneca AB
SE-151 85 Södertälje, Sweden

Distributed by:
ANI Pharmaceuticals, Inc.
Baudette, MN 56623

ATACAND is a registered trademark of the AstraZeneca group of companies and is licensed to ANI Pharmaceuticals, Inc.

All brand names listed are the registered trademarks of their respective owners and are not trademarks of ANI Pharmaceuticals, Inc.

Issued: 07/2025

PRINCIPAL DISPLAY PANEL – 4 mg

NDC 62559-640-30
ATACAND® (candesartan cilexetil) Tablets
4 mg
Rx only
30 Tablets

PRINCIPAL DISPLAY PANEL – 8 mg

NDC 62559-641-30
ATACAND® (candesartan cilexetil) Tablets
8 mg
Rx only
30 Tablets

PRINCIPAL DISPLAY PANEL – 16 mg

NDC 62559-642-30
ATACAND® (candesartan cilexetil) Tablets
16 mg
Rx only
30 Tablets

PRINCIPAL DISPLAY PANEL – 32 mg

NDC 62559-643-30
ATACAND® (candesartan cilexetil) Tablets
32 mg
Rx only
30 Tablets